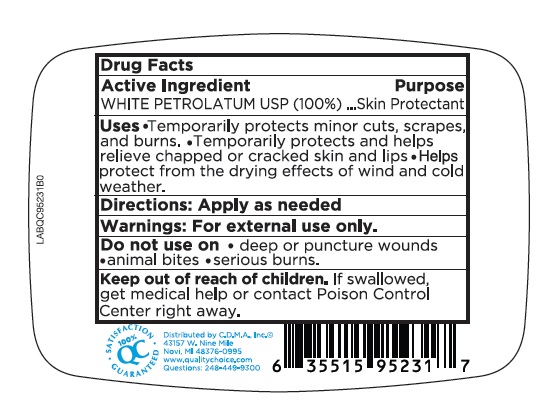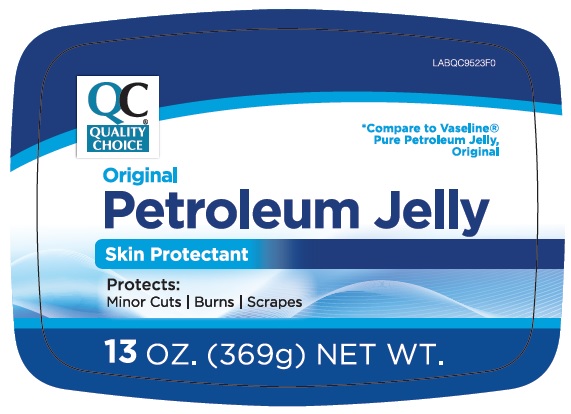 DRUG LABEL: Original Petroleum
NDC: 42669-211 | Form: JELLY
Manufacturer: Davion, Inc.
Category: otc | Type: HUMAN OTC DRUG LABEL
Date: 20221205

ACTIVE INGREDIENTS: PETROLATUM 100 g/100 g

Original Petroleum Jelly

Active Ingredient

WHITE PETROLATUM, USP (100%)

Purpose

Skin Protectant

Uses

- Temporarily protects minor, cuts, scrapes, and burns
- Temporarily protects and helps relieve chapped or cracked skin and lips
- Helps protect from the drying effects of wind and cold weather

Directions:

Apply as needed

Warnings:

For External Use Only

Do not use on

- deep or puncture wounds
- animal bites
- serious burns

Keep out of reach of children.

If swallowed get medical help or contact a Poison Control Center right away.

Package Display

Original Petroleum Jelly

Skin Protectant

Protects:

- Minor Cuts
- Burns
- Scrapes

13 oz. (369 g)